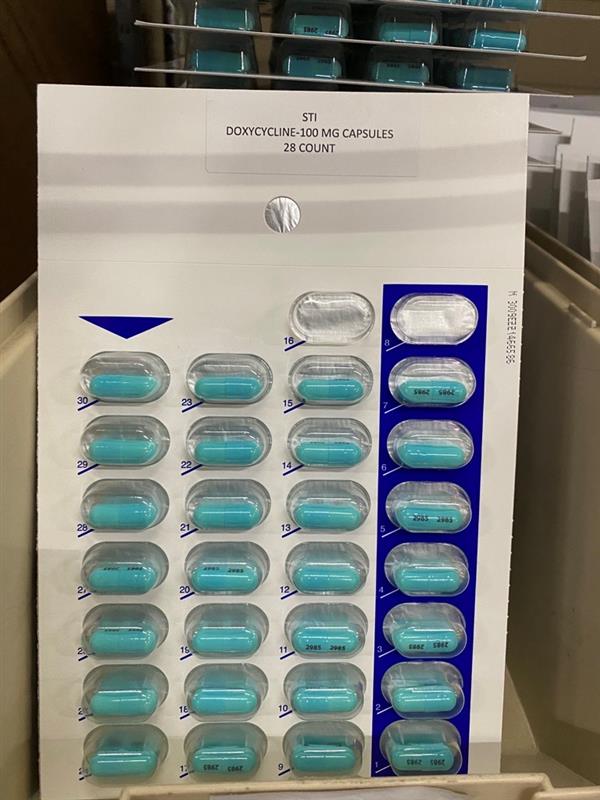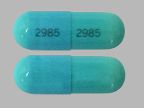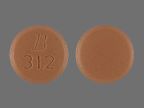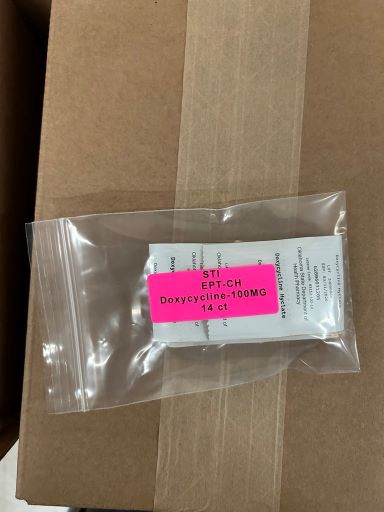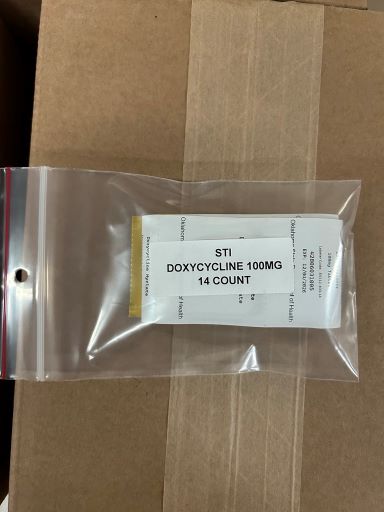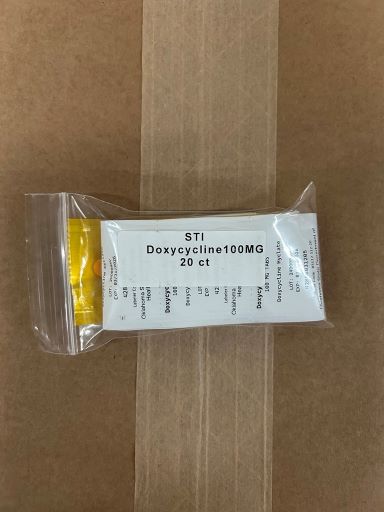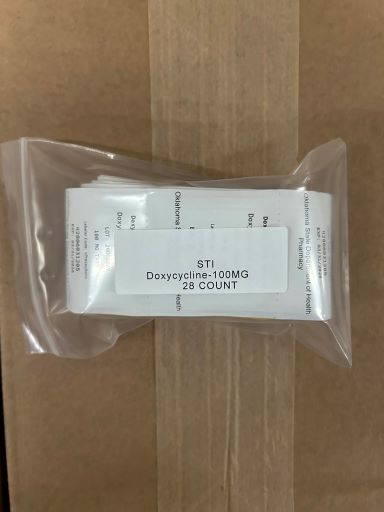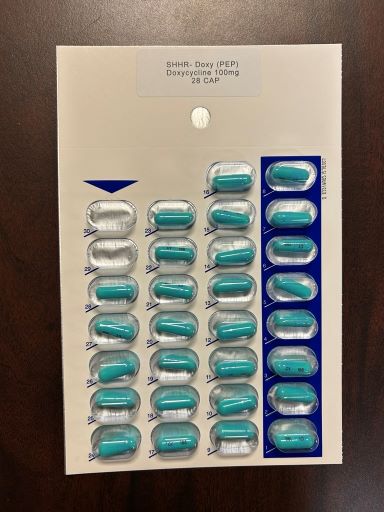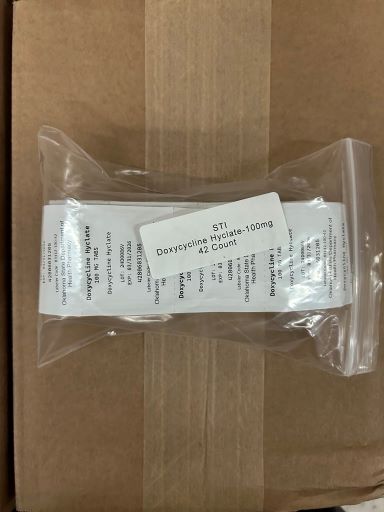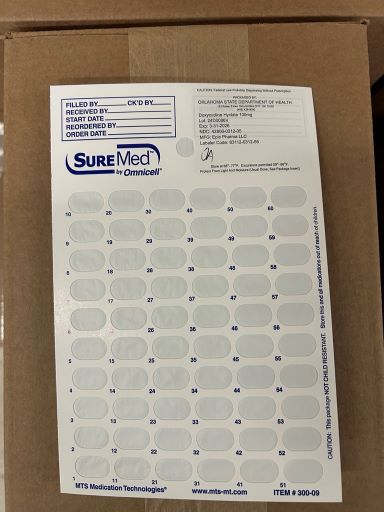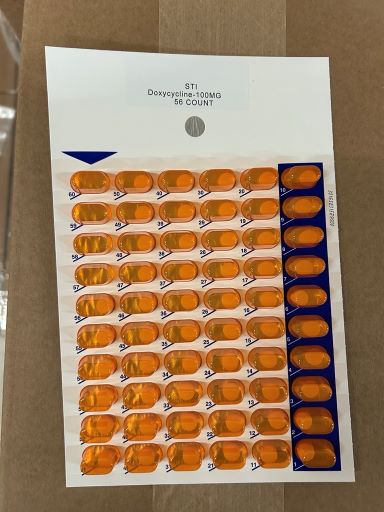 DRUG LABEL: Doxycycline
NDC: 83112-233 | Form: CAPSULE
Manufacturer: Health Department, Oklahoma State
Category: prescription | Type: HUMAN PRESCRIPTION DRUG LABEL
Date: 20251231

ACTIVE INGREDIENTS: DOXYCYCLINE HYCLATE 100 mg/1 1

Doxycycline Hyclate

Doxycycline Hyclate 100 mg Warnings Section

The use of drugs of the tetracycline class during tooth development (last half of pregnancy, infancy and childhood to the age of 8 years) may cause permanent discoloration of the teeth (yellow-gray-brown). This adverse reaction is more common during long-term use of the drugs, but it has been observed following repeated short-term courses. Enamel hypoplasia has also been reported. Use doxycycline in pediatric patients 8 years of age or less only when the potential benefits are expected to outweigh the risks in severe or life-threatening conditions (e.g., anthrax, Rocky Mountain spotted fever), particularly when there are no alternative therapies.

Clostridium difficile associated diarrhea (CDAD) has been reported with use of nearly all antibacterial agents, including doxycycline, and may range in severity from mild diarrhea to fatal colitis. Treatment with antibacterial agents alters the normal flora of the colon leading to overgrowth of C. difficile.

C. difficile produces toxins A and B which contribute to the development of CDAD. Hypertoxin producing strains of C. difficile cause increased morbidity and mortality, as these infections can be refractory to antimicrobial therapy and may require colectomy. CDAD must be considered in all patients who present with diarrhea following the use of antibacterial drugs. Careful medical history is necessary since CDAD has been reported to occur over two months after the administration of antibacterial agents.

If CDAD is suspected or confirmed, ongoing use of antibacterial drugs not directed against C. difficile may need to be discontinued. Appropriate fluid and electrolyte management, protein supplementation, antibacterial treatment of C. difficile, and surgical evaluation should be instituted as clinically indicated.

Severe skin reactions, such as exfoliative dermatitis, erythema multiforme, Stevens-Johnson syndrome, toxic epidermal necrolysis, and drug reaction with eosinophilia and systemic symptoms (DRESS) have been reported in patients receiving doxycycline. (See ADVERSE REACTIONS.) If severe skin reactions occur, doxycycline should be discontinued immediately and appropriate therapy should be instituted.

Intracranial hypertension (IH, pseudotumor cerebri) has been associated with the use of tetracyclines including doxycycline. Clinical manifestations of IH include headache, blurred vision, diplopia, and vision loss; papilledema can be found on fundoscopy. Women of childbearing age who are overweight or have a history of IH are at greater risk for developing tetracycline associated IH. Concomitant use of isotretinoin and doxycycline should be avoided because isotretinoin is also known to cause pseudotumor cerebri.

Although IH typically resolves after discontinuation of treatment, the possibility for permanent visual loss exists. If visual disturbance occurs during treatment, prompt ophthalmologic evaluation is warranted. Since intracranial pressure can remain elevated for weeks after drug cessation patients should be monitored until they stabilize.

All tetracyclines form a stable calcium complex in any bone-forming tissue. A decrease in fibula growth rate has been observed in prematures given oral tetracycline in doses of 25 mg/kg every 6 hours. This reaction was shown to be reversible when the drug was discontinued.

Results of animal studies indicate that tetracyclines cross the placenta, are found in fetal tissues, and can have toxic effects on the developing fetus (often related to retardation of skeletal development). Evidence of embryotoxicity has also been noted in animals treated early in pregnancy. If any tetracycline is used during pregnancy or if the patient becomes pregnant while taking this drug, the patient should be apprised of the potential hazard to the fetus.

The antianabolic action of the tetracyclines may cause an increase in BUN. Studies to date indicate that this does not occur with the use of doxycycline in patients with impaired renal function.

Photosensitivity manifested by an exaggerated sunburn reaction has been observed in some individuals taking tetracyclines. Patients apt to be exposed to direct sunlight or ultraviolet light should be advised that this reaction can occur with tetracycline drugs, and treatment should be discontinued at the first evidence of skin erythema.